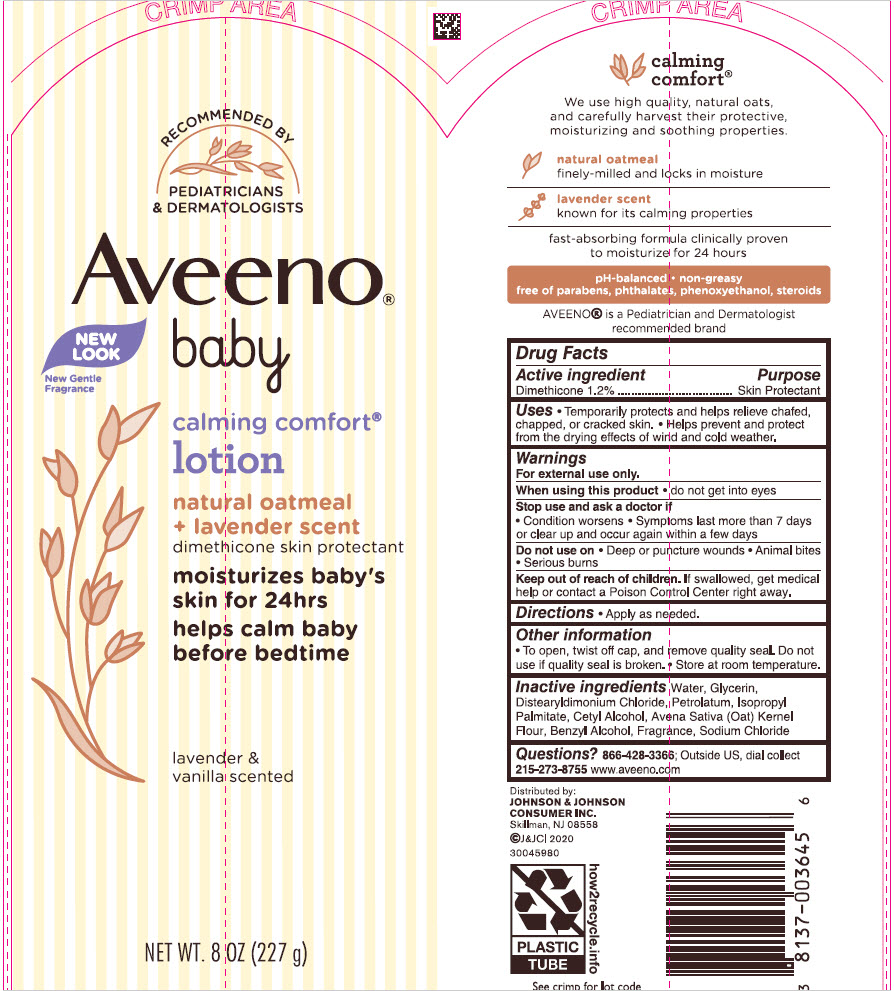 DRUG LABEL: Aveeno Baby Calming Comfort
NDC: 69968-0656 | Form: LOTION
Manufacturer: Kenvue Brands LLC
Category: otc | Type: HUMAN OTC DRUG LABEL
Date: 20241105

ACTIVE INGREDIENTS: DIMETHICONE 12 mg/1 g
INACTIVE INGREDIENTS: GLYCERIN; WATER; DISTEARYLDIMONIUM CHLORIDE; PETROLATUM; ISOPROPYL PALMITATE; CETYL ALCOHOL; OATMEAL; BENZYL ALCOHOL; SODIUM CHLORIDE

Aveeno® Baby Calming Comfort® Lotion

Drug Facts

Active ingredient

Dimethicone 1.2%

Purpose

Skin Protectant

Uses

- Temporarily protects and helps relieve chafed, chapped, or cracked skin
- Helps prevent and protect from the drying effects of wind and cold weather.

Warnings

For external use only.

When using this product

- Do not get into eyes.

Stop use and ask a doctor if

- Condition worsens
- Symptoms last more than 7 days or clear up and occur again within a few days.

Do not use on

- Deep or puncture wounds
- Animal bites
- Serious burns .

Keep out of reach of children. If swallowed, get medical help or contact a Poison Control Center right away.

Directions

- Apply as needed.

Other information

- To open, twist off cap, and remove quality seal. Do not use if quality seal is broken.
- Store at room temperature.

Inactive ingredients

Water , Glycerin, Distearyldimonium Chloride, Petrolatum, Isopropyl Palmitate, Cetyl Alcohol, Avena Sativa (Oat) Kernel Flour, Benzyl Alcohol, Fragrance, Sodium Chloride

Questions?

866-428-3366; Outside US, dial collect 215-273-8755 www.aveeno.com

Distributed by:
JOHNSON & JOHNSON
CONSUMER INC.
Skillman, NJ 08558

PRINCIPAL DISPLAY PANEL - 227 g Tube Label

RECOMMENDED BY
PEDIATRICIANS
& DERMATOLOGISTS

Aveeno®
Baby
NEW
LOOK
New Gentle
Fragrance

calming comfort®
lotion

natural oatmeal
+ lavender scent

dimethicone skin protectant

moisturizes baby's
skin for 24hrs
helps calm baby
before bedtime

lavender &
vanilla scented

NET WT. 8 OZ (227 g)